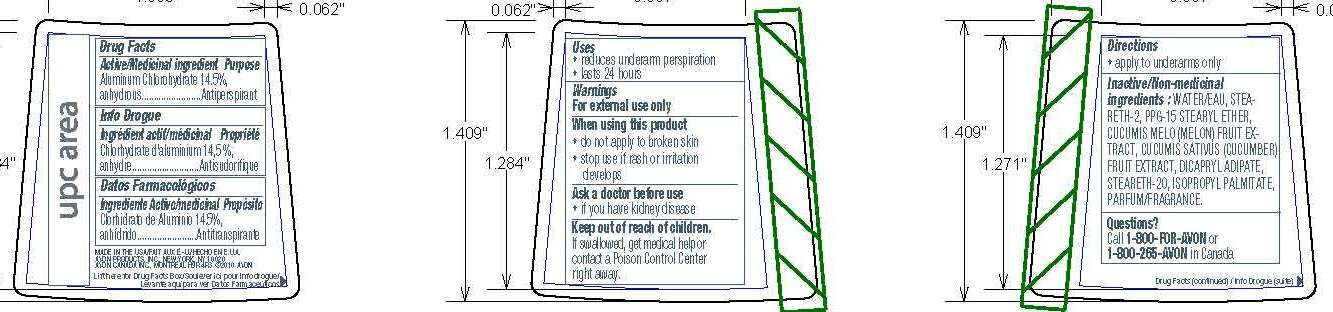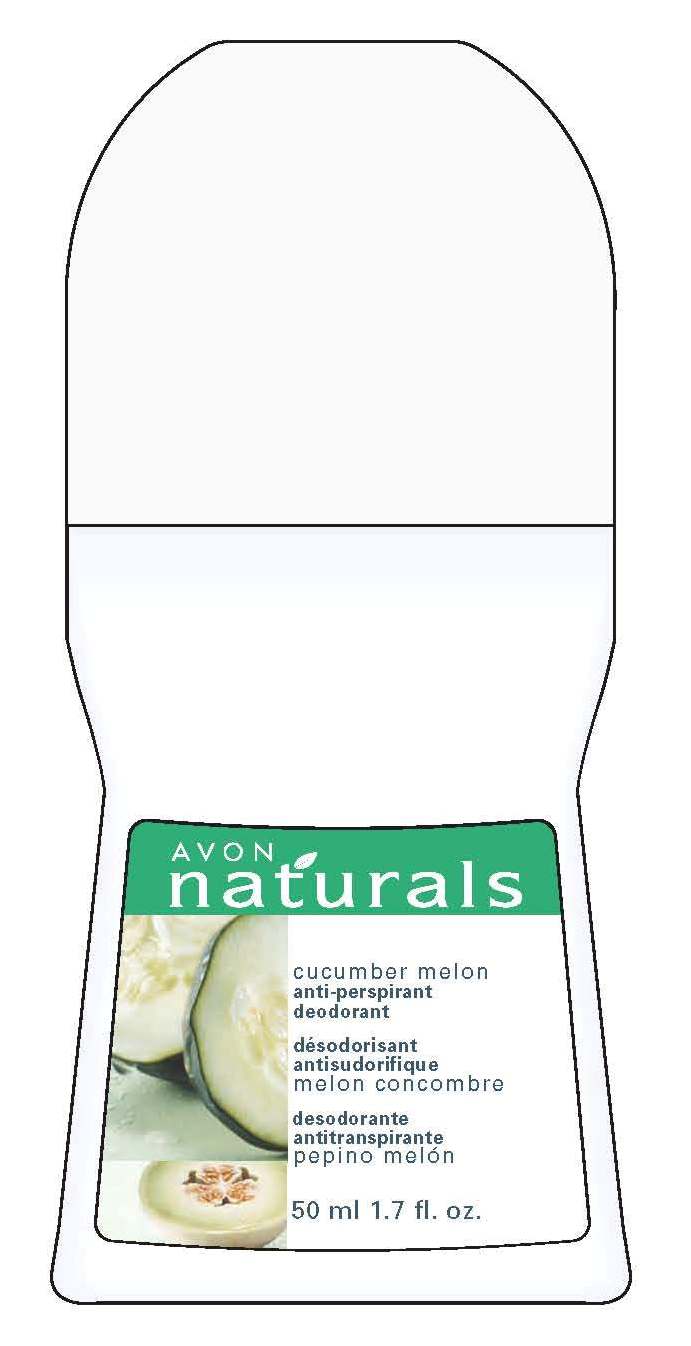 DRUG LABEL: Naturals
NDC: 10096-0219 | Form: GEL
Manufacturer: Avon Products, Inc.
Category: otc | Type: HUMAN OTC DRUG LABEL
Date: 20100611

ACTIVE INGREDIENTS: Aluminum Chlorohydrate 7.25 mL/50 mL
INACTIVE INGREDIENTS: WATER; STEARETH-2; STEARETH-20; ISOPROPYL PALMITATE

Drug Facts

Active/
Medicinal ingredient Purpose
Aluminum Chlorohydrate
14.5%, anhydrous...................Antiperspirant

Uses
• reduces underarm perspiration
• lasts 24 hours

Warnings
For external use only

When using this product
• do not apply to broken skin
• stop use if rash or irritation develops

Ask a doctor before use
• if you have kidney disease

Keep out of reach of children.
If swallowed, get medical help or
contact a Poison Control Center
right away.

Directions
• apply to underarms only

Inactive/Non-medicinal Ingredients:

WATER/EAU
STEARETH-2
PPG-15 STEARYL ETHER
CUCUMIS MELO (MELON) FRUIT EXTRACT
CUCUMIS SATIVUS (CUCUMBER) FRUIT EXTRACT
DICAPRYL ADIPATE
STEARETH-20
ISOPROPYL PALMITATE
PARFUM/FRAGRANCE

Questions? Call 1-800-FOR-AVON
or 1-800-265-AVON in Canada